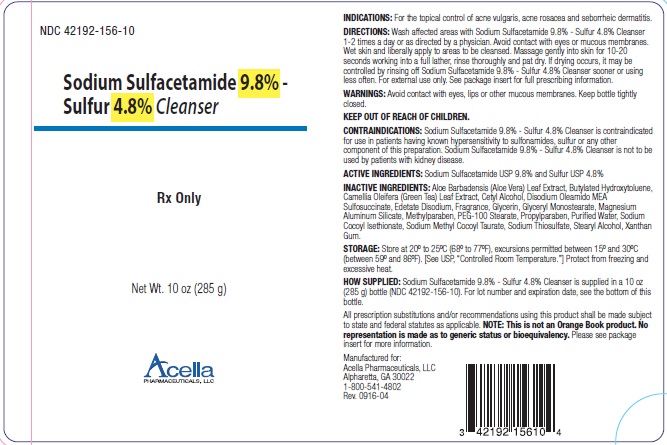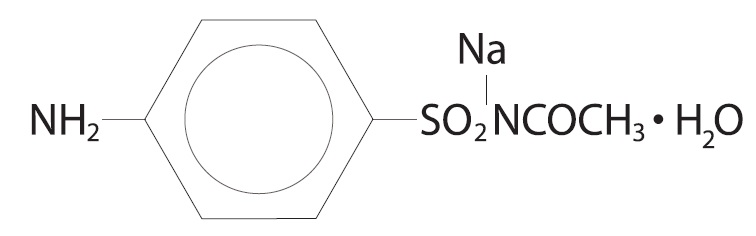 DRUG LABEL: Sodium Sulfacetamide 9.8% and Sulfur 4.8% Cleanser
NDC: 42192-156 | Form: LIQUID
Manufacturer: Acella Pharmaceuticals, LLC
Category: prescription | Type: HUMAN PRESCRIPTION DRUG LABEL
Date: 20240115

ACTIVE INGREDIENTS: SULFACETAMIDE SODIUM 98 mg/1 g; SULFUR 48 mg/1 g
INACTIVE INGREDIENTS: ALOE VERA LEAF; BUTYLATED HYDROXYTOLUENE; CAMELLIA OLEIFERA LEAF; CETYL ALCOHOL; DISODIUM OLEAMIDO MONOETHANOLAMINE SULFOSUCCINATE; EDETATE DISODIUM; GLYCERIN; GLYCERYL MONOSTEARATE; MAGNESIUM ALUMINUM SILICATE; METHYLPARABEN; PEG-100 STEARATE; PROPYLPARABEN; WATER; SODIUM COCOYL ISETHIONATE; SODIUM METHYL COCOYL TAURATE; SODIUM THIOSULFATE; STEARYL ALCOHOL; XANTHAN GUM

Sodium Sulfacetamide 9.8% - Sulfur 4.8% Cleanser

Rx Only

DESCRIPTION

Each gram of Sodium Sulfacetamide 9.8% - Sulfur 4.8% Cleanser contains 98 mg of Sodium Sulfacetamide and 48 mg of Sulfur in a formulation containing Aloe Barbadensis (Aloe Vera) Leaf Extract, Butylated Hydroxytoluene, Camellia Oleifera (Green Tea) Leaf Extract, Cetyl Alcohol, Disodium Oleamido MEA Sulfosuccinate, Edetate Disodium, Fragrance, Glycerin, Glyceryl Monostearate, Magnesium Aluminum Silicate, Methylparaben, PEG-100 Stearate, Propylparaben, Purified Water, Sodium Cocoyl Isethionate, Sodium Methyl Cocoyl Taurate, Sodium Thiosulfate, Stearyl Alcohol and Xanthan Gum.

Sodium sulfacetamide is a sulfonamide with antibacterial activity while sulfur acts as a keratolytic agent.

Chemically sodium sulfacetamide is N-[(4-aminophenyl) sulfonyl]-acetamide, monosodium salt, monohydrate.

The structural formula is:

CLINICAL PHARMACOLOGY

The most widely accepted mechanism of action of sulfonamides is the Woods-Fildes theory, which is based on the fact that sulfonamides act as competitive antagonists to para-aminobenzoic acid (PABA), an essential component for bacterial growth. While absorption through intact skin has not been determined, sodium sulfacetamide is readily absorbed from the gastrointestinal tract when taken orally and excreted in the urine, largely unchanged. The biological half-life has variously been reported as 7 to 12.8 hours. The exact mode of action of sulfur in the treatment of acne is not known, but it has been reported that it inhibits the growth of Propionibacterium acnes and the formation of free fatty acids.

INDICATIONS

Sodium Sulfacetamide 9.8% - Sulfur 4.8% Cleanser is indicated in the topical control of acne vulgaris, acne rosacea and seborrheic dermatitis.

CONTRAINDICATIONS:

Sodium Sulfacetamide 9.8% - Sulfur 4.8% Cleanser is contraindicated for use by patients having known hypersensitivity to sulfonamides, sulfur or any other component of this preparation. Sodium Sulfacetamide 9.8% - Sulfur 4.8% Cleanser is not to be used by patients with kidney disease.

WARNINGS

Although rare, sensitivity to sodium sulfonamide may occur. Therefore, caution and careful supervision should be observed when prescribing this drug for patients who may be prone to hypersensitivity to topical sulfonamides. Systemic toxic reactions such as agranulocytosis, acute hemolytic anemia, purpura hemorrhagica, drug fever, jaundice and contact dermatitis indicate hypersensitivity to sulfonamides. Particular caution should be employed if areas of denuded or abraded skin are involved.
FOR EXTERNAL USE ONLY. Keep away from eyes. Keep out of reach of children. Keep container tightly closed.

PRECAUTIONS

General - If irritation develops, use of the product should be discontinued and appropriate therapy instituted. Patients should be carefully observed for possible local irritation or sensitization during long-term therapy. The object of this therapy is to achieve desquamation without irritation, but sodium sulfacetamide and sulfur can cause reddening and scaling of the epidermis. These side effects are not unusual in the treatment of acne vulgaris, but patients should be cautioned about the possibility.

Information for patients - Avoid contact with eyes, eyelids, lips and mucous membranes.

If accidental contact occurs, rinse with water. If excessive irritation develops, discontinue use and consult your physician.

Carcinogenesis, Mutagenesis and Impairment of Fertility - Long-term studies in animals have not been performed to evaluate carcinogenic potential.

Pregnancy

Category C. Animal reproduction studies have not been conducted with Sodium Sulfacetamide 9.8% - Sulfur 4.8% Cleanser. It is not known whether Sodium Sulfacetamide 9.8% - Sulfur 4.8% Cleanser can cause fetal harm when administered to a pregnant woman or can affect reproduction capacity. Sodium Sulfacetamide 9.8% - Sulfur 4.8% Cleanser should be given to a pregnant woman only if clearly needed.

Nursing Mothers

It is not known whether sodium sulfacetamide is excreted in the human milk following topical use of Sodium Sulfacetamide 9.8% - Sulfur 4.8% Cleanser. However, small amounts of orally administered sulfonamides have been reported to be eliminated in human milk. In view of this and because many drugs are excreted in human milk, caution should be exercised when Sodium Sulfacetamide 9.8% - Sulfur 4.8% Cleanser is administered to a nursing woman.

Pediatric Use

Safety and effectiveness in children under the age of 12 have not been established.

ADVERSE REACTIONS

Although rare, sodium sulfacetamide may cause local irritation.

DOSAGE AND ADMINISTRATION

Wash affected areas once or twice daily, or as directed by your physician. Avoid contact with eyes or mucous membranes. Wet skin and liberally apply to areas to be cleansed. Massage gently into skin for 10 to 20 seconds, working into a full lather, rinse thoroughly and pat dry. If skin dryness occurs, it may be controlled by rinsing off sooner or using less frequently.

HOW SUPPLIED

Sodium Sulfacetamide 9.8% - Sulfur 4.8% Cleanser is supplied in a 10 oz (285 g) bottle (NDC 42192-156-10).

STORAGE

Store at 20º to 25ºC (68º to 77ºF), excursions permitted between 15º and 30ºC (between 59º and 86ºF). [See USP, “Controlled Room Temperature.”] Protect from freezing and excessive heat.

KEEP THIS AND ALL MEDICATIONS OUT OF THE REACH OF CHILDREN.

All prescription substitutions using this product shall be made subject to state and federal statutes as applicable. NOTE: This is not an Orange Book product and has not been subjected to FDA therapeutic equivalency or other equivalency testing. No representation is made as to generic status or bioequivalency. Each person recommending a prescription substitution using this product shall make such recommendations based on each such person’s professional opinion and knowledge, upon evaluating the active ingredients, excipients, inactive ingredients and chemical formulation information provided herein.

MANUFACTURED FOR:
Acella Pharmaceuticals, LLC
Alpharetta, GA 30022
1-800-541-4802
Rev. 0916-04

PACKAGE LABEL

NDC 42192-156-10

Sodium Sulfacetamide 9.8% - Sulfur 4.8% Cleanser

Rx Only

Net Wt. 10 oz (285 g)

Acella Pharmaceuticals, LLC